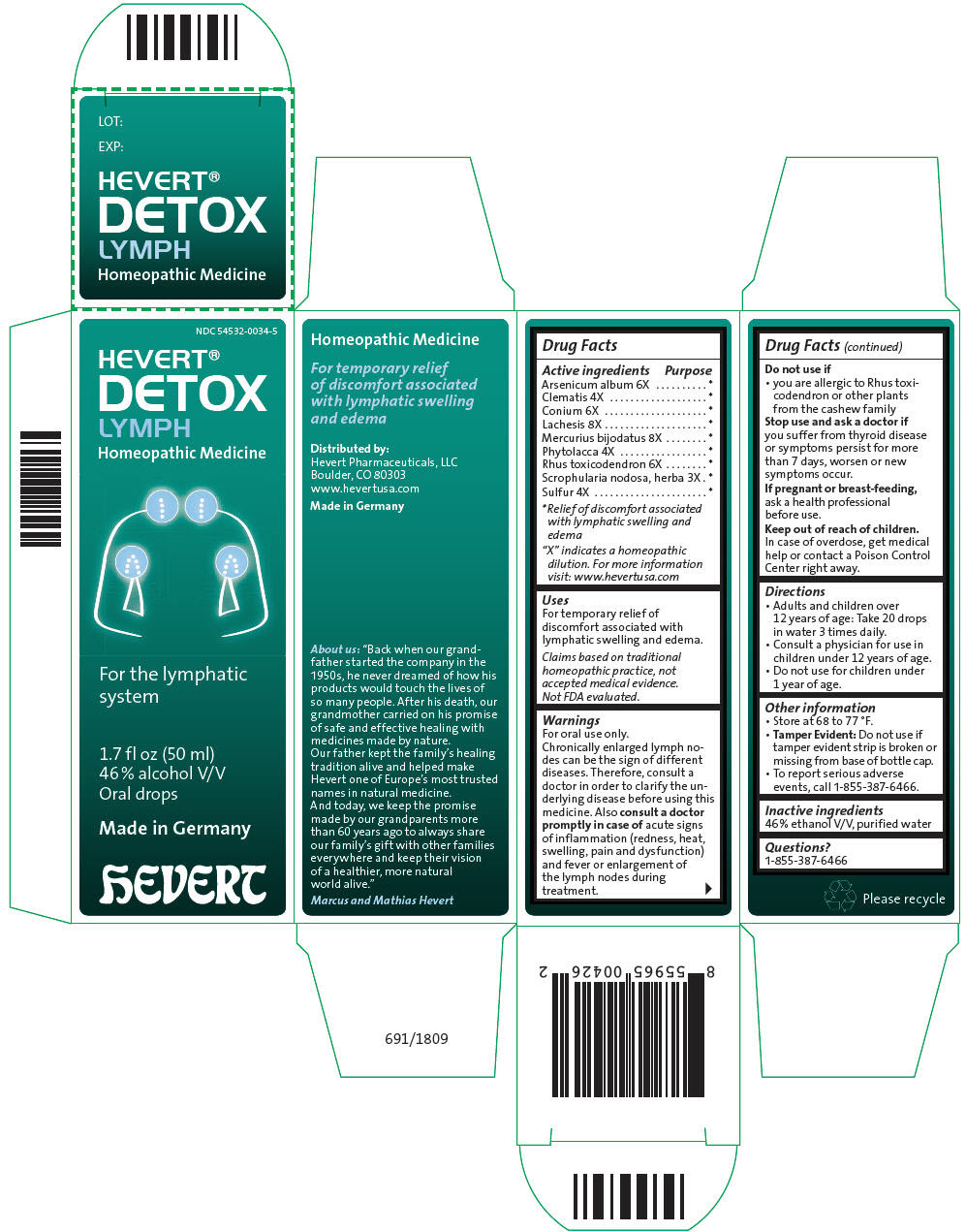 DRUG LABEL: Hevert Detox Lymph
NDC: 54532-0034 | Form: LIQUID
Manufacturer: Hevert Arzneimittel GmbH & Co KG
Category: homeopathic | Type: HUMAN OTC DRUG LABEL
Date: 20221220

ACTIVE INGREDIENTS: Arsenic Trioxide 6 [hp_X]/50 mL; Clematis Recta Flowering top 4 [hp_X]/50 mL; Conium Maculatum Flowering Top 6 [hp_X]/50 mL; Lachesis Muta Venom 8 [hp_X]/50 mL; Mercuric Iodide 8 [hp_X]/50 mL; Phytolacca Americana Root 4 [hp_X]/50 mL; Toxicodendron Pubescens shoot 6 [hp_X]/50 mL; Scrophularia Nodosa leaf with stem 3 [hp_X]/50 mL; Sulfur 4 [hp_X]/50 mL
INACTIVE INGREDIENTS: ALCOHOL; WATER

Hevert® Detox Lymph

Drug Facts

ACTIVE INGREDIENT

PURPOSE

Active ingredients

Purpose

Arsenicum album 6X

[Relief of discomfort associated with lymphatic swelling and edema]

Clematis 4X

Conium 6X

Lachesis 8X

Mercurius bijodatus 8X

Phytolacca 4X

Rhus toxicodendron 6X

Scrophularia nodosa, herba 3X

Sulfur 4X

"X" indicates a homeopathic dilution. For more information visit: www.hevertusa.com

Uses

For temporary relief of discomfort associated with lymphatic swelling and edema.

Claims based on traditional homeopathic practice, not accepted medical evidence. Not FDA evaluated.

Warnings

For oral use only.

ASK DOCTOR

Chronically enlarged lymph nodes can be the sign of different diseases. Therefore, consult a doctor in order to clarify the underlying disease before using this medicine. Also consult a doctor promptly in case of acute signs of inflammation (redness, heat, swelling, pain and dysfunction) and fever or enlargement of the lymph nodes during treatment.

Do not use if

- you are allergic to Rhus toxicodendron or other plants from the cashew family

Stop use and ask a doctor if you suffer from thyroid disease or symptoms persist for more than 7 days, worsen or new symptoms occur.

PREGNANCY OR BREAST FEEDING

If pregnant or breast-feeding, ask a health professional before use.

Keep out of reach of children. In case of overdose, get medical help or contact a Poison Control Center right away.

Directions

- Adults and children over 12 years of age: Take 20 drops in water 3 times daily.
- Consult a physician for use in children under 12 years of age.
- Do not use for children under 1 year of age.

Other information

- Store at 68 to 77 °F.
- Tamper Evident: Do not use if tamper evident strip is broken or missing from base of bottle cap.
- To report serious adverse events, call 1-855-387-6466.

Inactive ingredients

46 % ethanol V/V, purified water

Questions?

1-855-387-6466

Distributed by:
Hevert Pharmaceuticals, LLC
Boulder, CO 80303

PRINCIPAL DISPLAY PANEL - 50 ml Bottle Carton

NDC 54532-0034-5

HEVERT®
DETOX
LYMPH
Homeopathic Medicine

For the lymphatic
system

1.7 fl oz (50 ml)
46 % alcohol V/V
Oral drops

Made in Germany

hEVERT